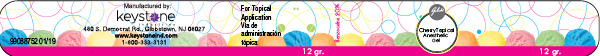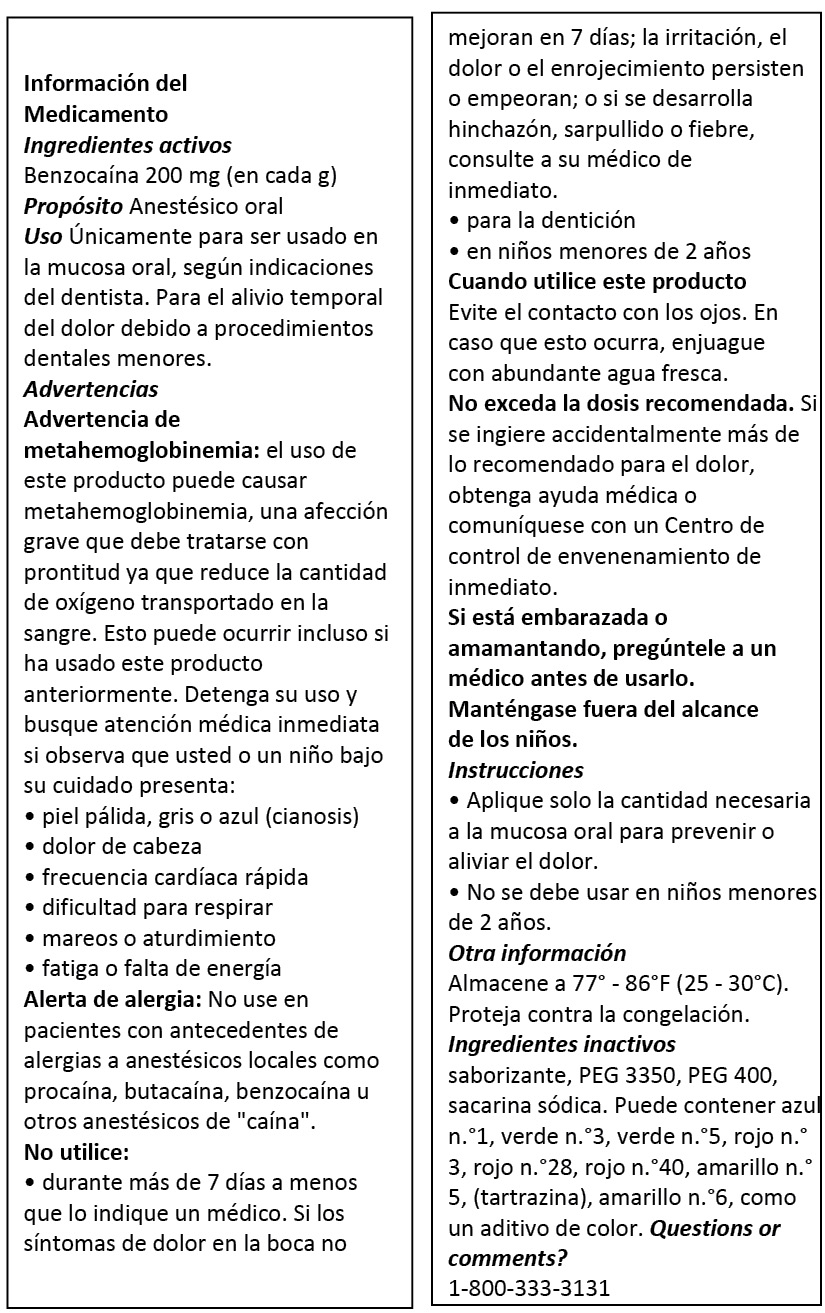 DRUG LABEL: Gelato Topical Anesthetic
NDC: 68400-501 | Form: GEL
Manufacturer: Mycone Dental Supply Co., Inc DBA Keystone Industries and Deepak Products Inc.
Category: prescription | Type: HUMAN PRESCRIPTION DRUG LABEL
Date: 20251113

ACTIVE INGREDIENTS: BENZOCAINE 2.4 g/12 g
INACTIVE INGREDIENTS: POLYETHYLENE GLYCOL 400; POLYETHYLENE GLYCOL 3350; SACCHARIN SODIUM; FD&C YELLOW NO. 5; FD&C YELLOW NO. 6; FD&C RED NO. 3; FD&C RED NO. 40; FD&C BLUE NO. 1; FD&C GREEN NO. 3; D&C RED NO. 28; D&C GREEN NO. 5

Ingredientes activos

Benzocaína 200 mg (en cada g)

Propósito

Anestésico oral

Uso

Únicamente para ser usado en la mucosa oral, según indicaciones
del dentista. Para el alivio temporal del dolor debido a procedimientos dentales menores.

Advertencias

Advertencia de metahemoglobinemia: el uso de este producto puede causar metahemoglobinemia, una afección grave que debe tratarse con pron_tud ya que reduce la cantidad de oxígeno transportado en la sangre. Esto puede ocurrir incluso si ha usado este product anteriormente. Detenga su uso y busque atención médica inmediata si observa que usted o un niño bajo su cuidado presenta:
• piel pálida, gris o azul (cianosis)
• dolor de cabeza
• frecuencia cardíaca rápida
• dificultad para respirar
• mareos o aturdimiento
• fatiga o falta de energía

Alerta de alergia:
No use en pacientes con antecedentes de alergias a anestésicos locales como procaína, butacaína, benzocaína u otros anestésicos de "caína".

No utilice:
• durante más de 7 días a menos que lo indique un médico. Si los síntomas de dolor en la boca no mejoran en 7 días; la irritación, el dolor o el enrojecimiento persisten o empeoran; o si se desarrolla hinchazón, sarpullido o fiebre, consulte a su médico de inmediato.
• para la dentición
• en niños menores de 2 años

Cuando utilice este producto
Evite el contacto con los ojos. En caso que esto ocurra, enjuague con abundante agua fresca.

No exceda la dosis recomendada.
Si se ingiere accidentalmente más de lo recomendado para el dolor, obtenga ayuda médica o
comuníquese con un Centro de control de envenenamiento de inmediato.

KEEP OUT OF REACH OF CHILDREN

Si está embarazada o amamantando, pregúntele a un médico antes de usarlo. Manténgase fuera del alcance de los niños.

Instrucciones

• Aplique solo la cantidad necesaria a la mucosa oral para prevenir o aliviar el dolor.
• No se debe usar en niños menores de 2 años.

Otra información

Almacene a 77° - 86°F (25 - 30°C). Proteja contra la congelación.

Ingredientes inactivos

saborizante, PEG 3350, PEG 400, sacarina sódica. Puede contener azul n.°1, verde n.°3, verde n.°5, rojo n. ° 3, rojo n.°28, rojo n.°40, Amarillo n.°5, (tartrazina), amarillo n.°6, como un aditivo de color.

Questions or comments?

1-800-333-3131